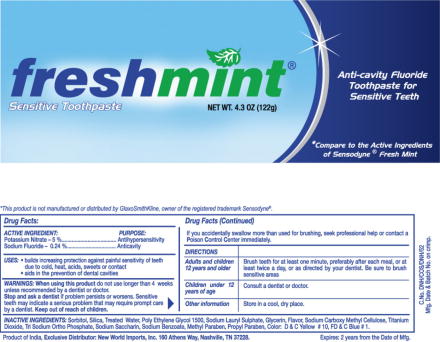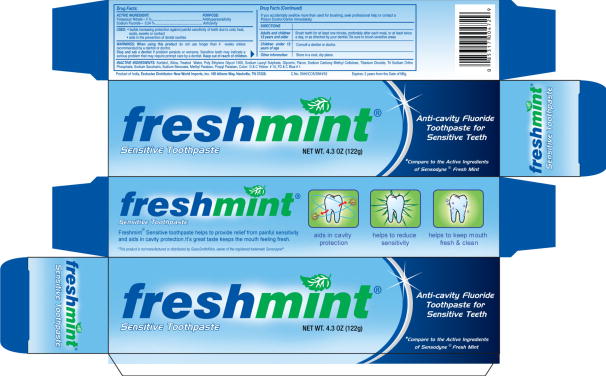 DRUG LABEL: Freshmint Sensitive Toothpaste
NDC: 68747-6031 | Form: PASTE, DENTIFRICE
Manufacturer: Dabur India Limited
Category: otc | Type: HUMAN OTC DRUG LABEL
Date: 20080825

ACTIVE INGREDIENTS: SODIUM FLUORIDE 2.4 mg/1 g; POTASSIUM NITRATE 50 mg/1 g
INACTIVE INGREDIENTS: SORBITOL; SILICON DIOXIDE; WATER; POLYETHYLENE GLYCOL 1500; SODIUM LAURYL SULFATE; GLYCERIN; CARBOXYMETHYLCELLULOSE SODIUM; TITANIUM DIOXIDE; SODIUM PHOSPHATE, TRIBASIC, DODECAHYDRATE; SACCHARIN SODIUM; SODIUM BENZOATE; METHYLPARABEN; PROPYLPARABEN

Sensodyne®

Drug Facts:

ACTIVE INGREDIENT

Potassium Nitrate - 5 %
Sodium Fluoride - 0.24 %

PURPOSE

Antihypersensitivity
Anticavity

USES

- builds increasing protection against painful sensitivity of teeth due to cold, heat, acids, sweets or contact
- aids in the prevention of dental cavities

WARNINGS

When using this product do not use longer than 4 weeks unless recommended by a dentist or doctor.

Stop and ask a dentist if problem persists or worsens. Sensitive teeth may indicate a serious problem that may require prompt care by a dentist. Keep out of reach of children.

If you accidentally swallow more than used for brushing, seek professional help or contact a Poison Control Center immediately.

DIRECTIONS

Adults and children 12 years and older

Brush teeth for at least one minute, preferably after each meal, or at least twice a day, or as directed by your dentist. Be sure to brush sensitive areas

Children under 12 years of age

Consult a dentist or doctor.

Other information

Store In a cool dry place.

INACTIVE INGREDIENT

INACTIVE INGREDIENTS: Sorbitol, Silica, Treated Water, Poly Ethylene Glycol 1500, Sodium Lauryl Sulphate, Glycerin, Flavor, Sodium Carboxy Methyl Cellulose, Titanium Dioxide, Tri Sodium Ortho Phosphate, Sodium Saccharin, Sodium Benzoate, Methyl Paraben, Propyl Paraben, Color D & C Yellow # 10, FD & C Blue # 1.

PACKAGE LABEL

Principal Display Panel - NET WT. 4.3 OZ (122g)

Freshmint Sensitive Toothpaste Tube Label
freshmint®

Sensitive Toothpaste NET WT. 4.3 OZ (122g)

Anti-cavity Fluoride Tootpaste for Sensitive
*Compare to the Active Ingredients of Sensodyne® Fresh Mint

Freshmint Sensitive Toothpaste Carton Label
freshmint®

Sensitive Toothpaste NET WT. 4.3 OZ (122g)

Anti-cavity Fluoride Tootpaste for Sensitive
*Compare to the Active Ingredients of Sensodyne® Fresh Mint